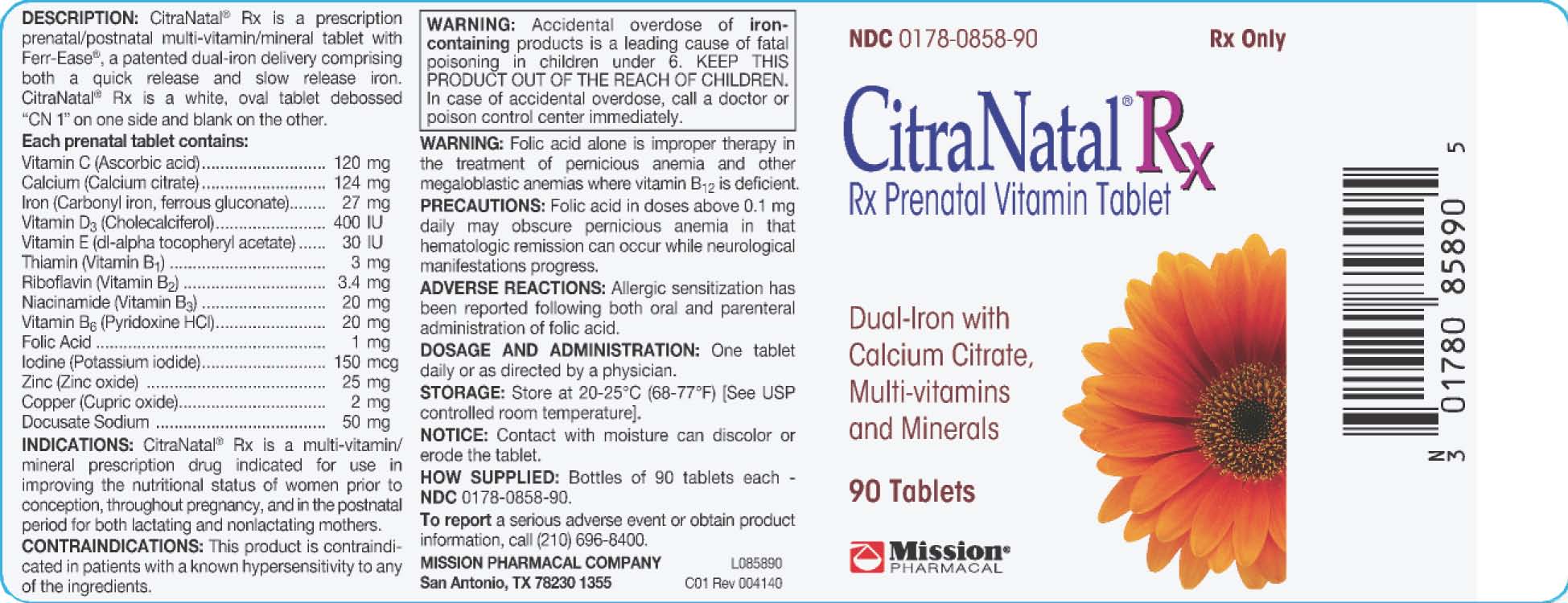 DRUG LABEL: CitraNatal Rx
NDC: 0178-0858 | Form: TABLET
Manufacturer: Mission Pharmacal Company
Category: prescription | Type: HUMAN PRESCRIPTION DRUG LABEL
Date: 20140804

ACTIVE INGREDIENTS: ASCORBIC ACID 120 mg/1 1; CALCIUM CITRATE 124 mg/1 1; IRON 27 mg/1 1; VITAMIN D 400 [iU]/1 1; .ALPHA.-TOCOPHEROL ACETATE 30 [iU]/1 1; THIAMINE 3 mg/1 1; RIBOFLAVIN 3.4 mg/1 1; NIACINAMIDE 20 mg/1 1; PYRIDOXINE HYDROCHLORIDE 20 mg/1 1; FOLIC ACID 1 mg/1 1; POTASSIUM IODIDE 150 mg/1 1; ZINC OXIDE 25 mg/1 1; CUPRIC OXIDE 2 mg/1 1
INACTIVE INGREDIENTS: POVIDONES 132.2 mg/1 1; DOCUSATE SODIUM 56.1 mg/1 1; CROSCARMELLOSE SODIUM 30.6 mg/1 1; TITANIUM DIOXIDE 30.5 mg/1 1; MAGNESIUM SILICATE 10.38 mg/1 1; MAGNESIUM STEARATE 5.1 mg/1 1; SHELLAC 2.59 mg/1 1; POLYETHYLENE GLYCOLS 1.98 mg/1 1; ETHYL VANILLIN .66 mg/1 1; VITAMIN A PALMITATE .15 mg/1 1

CitraNatal® Rx

DESCRIPTION

CitraNatal® Rx is a prenatal/postnatal multi-vitamin/mineral tablet with Ferr-Ease®, a patented dual-iron delivery comprising both a quick release and slow release iron. CitraNatal® Rx is a white, oval tablet debossed “CN 1” on one side and blank on the other.

Each prenatal tablet contains:
Vitamin C (Ascorbic acid) | ..............................................................................120 mg
Calcium (Calcium citrate) | ..............................................................................124 mg
Iron (Carbonyl iron, ferrous gluconate) | ..............................................................................27 mg
Vitamin D3 (Cholecalciferol) | ..............................................................................400 IU
Vitamin E (dl-alpha tocopheryl acetate) | ..............................................................................30 IU
Thiamin (Vitamin B1) | ..............................................................................3 mg
Riboflavin (Vitamin B2) | ..............................................................................3.4 mg
Niacinamide (Vitamin B3) | ..............................................................................20 mg
Vitamin B6 (Pyridoxine) | ..............................................................................20 mg
Folic Acid | ..............................................................................1 mg
Iodine (Potassium iodide) | ..............................................................................150 mcg
Zinc (Zinc oxide) | ..............................................................................25 mg
Copper (Cupric oxide) | ..............................................................................2 mg
Docusate Sodium | ..............................................................................50 mg

INDICATIONS

CitraNatal® Rx is a multi-vitamin/mineral prescription drug indicated for use in improving the nutritional status of women prior to conception, throughout pregnancy, and in the postnatal period for both lactating and nonlactating mothers.

CONTRAINDICATIONS

This product is contraindicated in patients with a known hypersensitivity to any of the ingredients.

BOXED WARNING

Accidental overdose of iron-containing products is a leading cause of fatal poisoning in children under 6. KEEP THIS PRODUCT OUT OF THE REACH OF CHILDREN. In case of accidental overdose, call a doctor or poison control center immediately.

WARNING

Folic acid alone is improper therapy in the treatment of pernicious anemia and other megaloblastic anemias where vitamin B12 is deficient.

PRECAUTIONS

Folic acid in doses above 0.1 mg daily may obscure pernicious anemia in that hematologic remission can occur while neurological manifestations progress.

ADVERSE REACTIONS

Allergic sensitization has been reported following both oral and parenteral administration of folic acid.

DOSAGE AND ADMINISTRATION

One tablet daily or as directed by a physician.

STORAGE

Store at 20-25°C (68-77°F) [See USP controlled room temperature].

NOTICE

Contact with moisture can discolor or erode the tablet.

HOW SUPPLIED

Bottles of 90 tablets each - NDC 0178-0858-90.

To report a serious adverse event or obtain product information, call (210) 696-8400.

MISSION PHARMACAL COMPANY L085890
San Antonio, TX USA 78230 1355 C01 Rev 004140

CitraNatal® Rx Label
NDC: 0178-0858-90